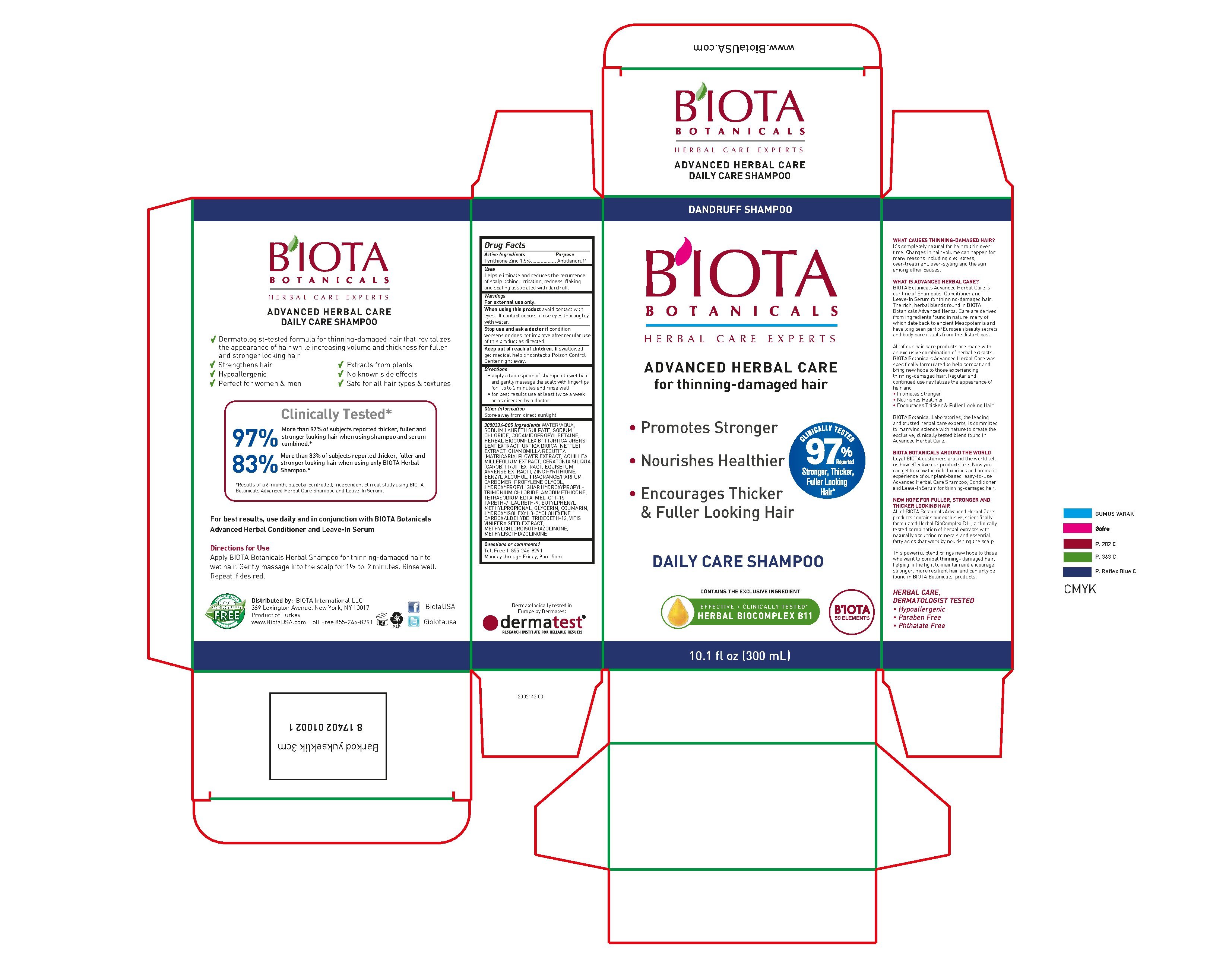 DRUG LABEL: Advanced Herbal Care
NDC: 23637-002 | Form: SHAMPOO
Manufacturer: B'IOTA Laboratories
Category: otc | Type: HUMAN OTC DRUG LABEL
Date: 20180116

ACTIVE INGREDIENTS: PYRITHIONE ZINC 0.15 g/1 mL
INACTIVE INGREDIENTS: WATER; SODIUM LAURETH SULFATE; SODIUM CHLORIDE; COCAMIDOPROPYL BETAINE; URTICA URENS LEAF; URTICA DIOICA ROOT; CHAMOMILE; ACHILLEA MILLEFOLIUM; CAROB; EQUISETUM ARVENSE TOP; BENZYL ALCOHOL; CARBOXYPOLYMETHYLENE; PROPYLENE GLYCOL; HYDROXYPROPYLTRIMONIUM CHLORIDE FRAGMENT; EDETATE SODIUM; HONEY; C11-15 PARETH-7; POLIDOCANOL; BUTYLPHENYL METHYLPROPIONAL; GLYCERIN; COUMARIN; HYDROXYISOHEXYL 3-CYCLOHEXENE CARBOXALDEHYDE; TRIDECETH-12; VITIS VINIFERA SEED; METHYLCHLOROISOTHIAZOLINONE; METHYLISOTHIAZOLINONE

ACTIVE INGREDIENT

Pyrithione Zinc 1.5%

PURPOSE

Pyrithione Zinc 1.5%.............Antidandruff

INDICATIONS AND USAGE

Helps eliminate and reduces the recurrence of scalp itching, irritation, redness, flaking and scaling associated with dandruff.

WARNINGS

For external use only.

When using this product avoid contact with eyes. If contact occurs, rinse eyes thoroughly with water.

Stop use and ask a doctor if condition worsens or does not improve after regular use of this product as directed.

Keep out of reach of children. If swallowed get medical help or contact a Poison Control Center right away.

Directions

- apply a tablespoon of shampoo to wet hair and gently massage the scalp with fingertips for 1.5 to 2 minutes and rinse well
- for best results use at least twice a week or as directed by a doctor

STORAGE AND HANDLING

Store away from direct sunlight

INACTIVE INGREDIENT

WATER/AQUA,SODIUM LAURETH SULFATE, SODIUM CHLORIDE, COCAMIDOPROPYL BETAINE, HERBAL BIOCOMPLEX B11 (URTICA URENS LEAF EXTRACT, URTICA DIOICA (NETTLE) EXTRACT, CHAMOMILLA RECUTITA (MATRICARIA) FLOWER EXTRACT, ACHILLEA MILLEFOLIUM EXTRACT, CERATONIA SILIQUA (CAROB) FRUIT EXTRACT, EQUISETUM ARVENSE EXTRACT), ZINC PYRITHIONE, BENZYL ALCOHOL, FRAGRANCE/PARFUM, CARBOMER, PROPYLENE GLYCOL, HYDROXYPROPYL GUAR HYDROXYPROPYLTRIMONIUM CHLORIDE, AMODIMETHICONE, TETRASODIUM EDTA, MEL, C11-15 PARETH-7, LAURETH-9, BUTYLPHENYL METHYLPROPIONAL, GLYCERIN, COUMARIN, HYDROXYISOHEXYL 3-CYCLOHEXENE CARBOXALDEHYDE, TRIDECETH-12, VITIS VINIFERA SEED EXTRACT, METHYLCHLOROISOTHIAZOLIN, METHYLISOTHIAZOLINONE

QUESTIONS

Toll Free 1-855-246-8291 Monday through Friday, 9am-5pm

DESCRIPTION

B'IOTA Botanicals Herbal Care Experts

Advanced Herbal Care Daily Care Shampoo

- Dermatolgist tested formulat for thinning-damaged hair that revitalizes the appearance of hair while increasing volume and thickness for fuller and stronger looking hair
- Strengthens hair
- Hypoallergenic
- Perfect for women & men
- Extracts from plants
- No known side effects
- Safe for all hair types & textures

Clinically Tested*
97% More than 97% of subjects reported thicker, fuller and stronger looking hair when using shampoo and serum combined.*
83% More than 83% of subjects reported thicker, fuller and stronger looking hair when using only BIOTA Herbal Shampoo.*
*Results of a 6-month, placebo-controlled, independent clinical study using BIOTA Botanicals Advanced Herbal Care Shampoo and Leave-In Serum.

For best results, use daily and in conjunction with BIOTA Botanicals Advanced Herbal Conditioner and Leave-In Serum

Directions for use

Apply BIOTA Botanicals Herbal Shampoo for thinning-damaged hair to wet hair. Gently massage into the scalp for 1 1/2-to-2 minutes. Rinse well. Repeat if desired.

Distributed by:
B'IOTA International LLC
369 Lexington Avenue, New York, NY 10017
Product of Turkey
www.biotaUSA.com
Toll Free 855-246-8291

DESCRIPTION

WHAT CAUSES THINNING-DAMAGED HAIR?

It’s completely natural for hair to thin over time. Changes in hair volume can happen for many reasons including diet, stress, over-treatment, over-styling and the sun among other causes.

WHAT IS ADVANCED HERBAL CARE?

BIOTA Botanicals Advanced Herbal Care is our line of Shampoos, Conditioner and Leave-In Serum for thinning-damaged hair. The rich, herbal blends found in BIOTA Botanicals Advanced Herbal Care are derived from ingredients found in nature, many of which date back to ancient Mesopotamia and have long been part of European beauty secrets and body care rituals from the distant past.

All of our hair care products are made with an exclusive combination of herbal extracts. BIOTA Botanicals Advanced Herbal Care was specifically formulated to help combat and bring new hope to those experiencing thinning-damaged hair. Regular and continued use revitalizes the appearance of hair and
• Promotes Stronger
• Nourishes Healthier
• Encourages Thicker & Fuller Looking Hair

BIOTA Botanical Laboratories, the leading and trusted herbal care experts, is committed to marrying science with nature to create the exclusive, clinically tested blend found in Advanced Herbal Care.

BIOTA BOTANICALS AROUND THE WORLD

Loyal BIOTA customers around the world tell us how effective our products are. Now you can get to know the rich, luxurious and aromatic experience of our plant-based, easy-to-use Advanced Herbal Care Shampoo, Conditioner and Leave-In Serum for thinning-damaged hair.

NEW HOPE FOR FULLER, STRONGER AND THICKER LOOKING HAIR

All of BIOTA Botanicals Advanced Herbal Care products contains our exclusive, scientificallyformulated Herbal BioComplex B11, a clinically tested combination of herbal extracts with naturally occurring minerals and essential fatty acids that work by nourishing the scalp.

This powerful blend brings new hope to those who want to combat thinning- damaged hair, helping in the fight to maintain and encourage
stronger, more resilient hair and can only be found in BIOTA Botanicals’ products.

HERBAL CARE,
DERMATOLOGIST TESTED
• Hypoallergenic
• Paraben Free
• Phthalate Free

PACKAGE LABEL

Dandruff Shampoo

B'IOTA BOTANICALS

ADVANCED HERBAL CARE

for thinning-damaged hair

- Promotes Stronger
- Nourishes Healthier
- Encourages Thicker & Fuller Looking Hair

Clinically Tested 97% reported Stronger, Thicker, Fuller Looking Hair*

Daily Care Shampoo

Contains the exclusive ingredient

Effective - Clinically Tested*

HERBAL BIOCOMPLEX B11

B'IOTA 59 Elements

10.1 fl oz (300 mL)